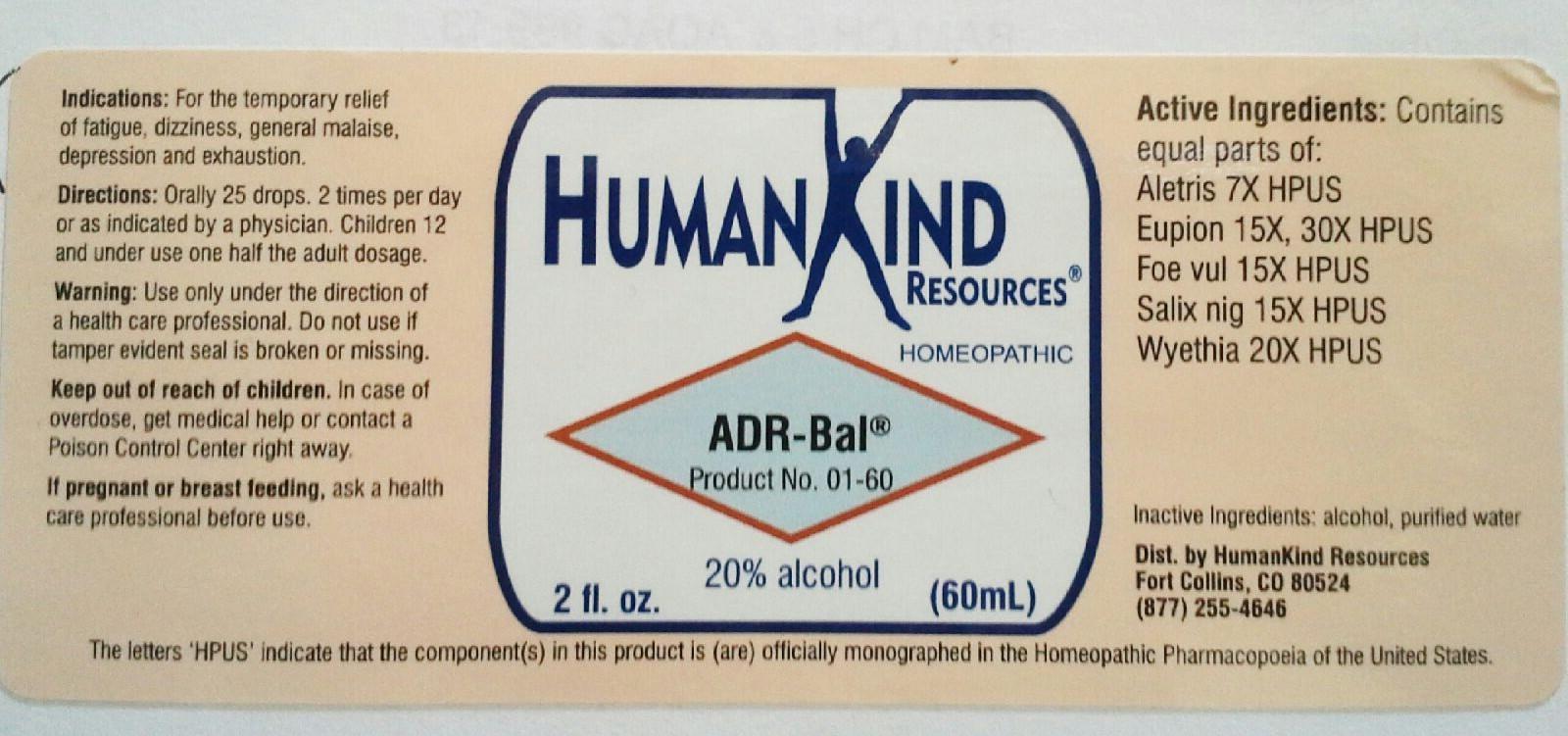 DRUG LABEL: ADR-Bal
NDC: 64616-079 | Form: LIQUID
Manufacturer: Vitality Works, Inc.
Category: homeopathic | Type: HUMAN OTC DRUG LABEL
Date: 20251217

ACTIVE INGREDIENTS: WOOD TAR HYDROCARBON DISTILLATE 15 [hp_X]/1 mL; ALETRIS FARINOSA ROOT 7 [hp_X]/1 mL; FENNEL SEED 15 [hp_X]/1 mL; SALIX NIGRA BARK 15 [hp_X]/1 mL; WYETHIA HELENIOIDES ROOT 20 [hp_X]/1 mL
INACTIVE INGREDIENTS: ALCOHOL; WATER

ADR-Bal

ADR-Bal

Alteris 7X

Eupion 15X, 30X

Foe vul 15X

Salix nig 15X

Wyethia 20X

ADR-Bal

Alcohol, Purified Water

ADR-Bal

Use only under the direction of a health care professional. Do not use if tamper evident seal is broken or missing.

ADR-Bal

Keep out of reach of children. In case of overdose, get medical help or contact a Poison Control Center right away.

ADR-Bal

For the temporary relief of fatigue, dizziness, general malaise, depression and exhaustion.

ADR-Bal

Orally 25 drops, 2 times per day or as indicated by a physician. Children 12 and under use one half the adult dosage.

ADR-Bal

Gland Re-Balance